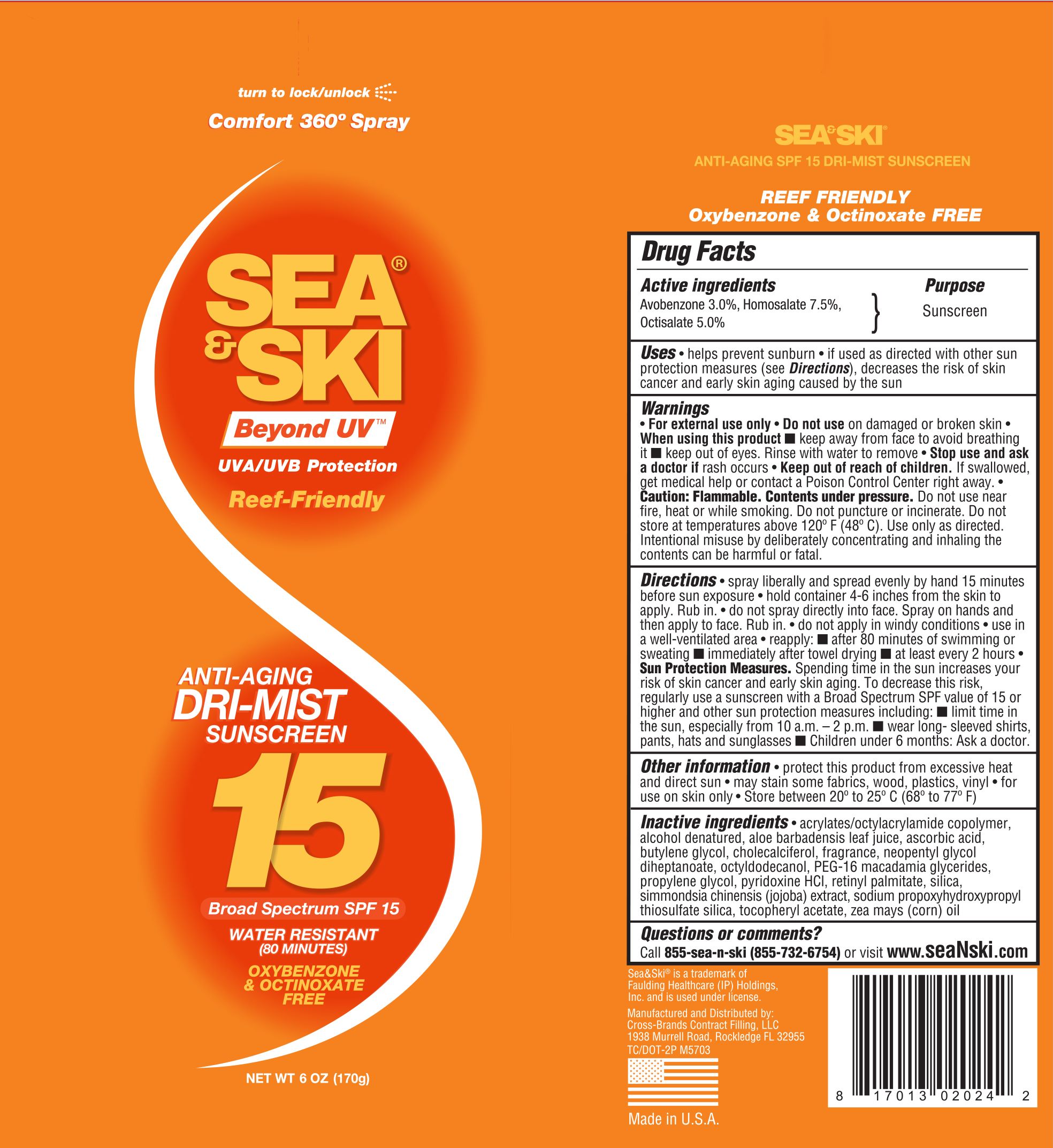 DRUG LABEL: Sea and Ski SPF 15 C-Spray
NDC: 73440-2024 | Form: AEROSOL, SPRAY
Manufacturer: Cross Brands Contract Filling
Category: otc | Type: HUMAN OTC DRUG LABEL
Date: 20210219

ACTIVE INGREDIENTS: AVOBENZONE 5.1 g/170 g; HOMOSALATE 12.75 g/170 g; OCTISALATE 8.5 g/170 g
INACTIVE INGREDIENTS: ALCOHOL 129.7 g/170 g

Sea and Ski SPF 15 C-Spray